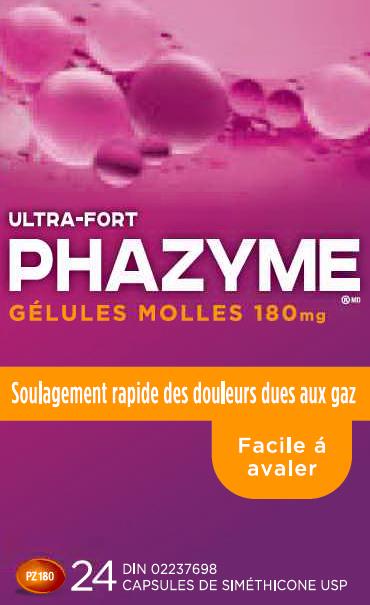 DRUG LABEL: PHAZYME
NDC: 0132-0210 | Form: CAPSULE, GELATIN COATED
Manufacturer: C.B. Fleet Company, Inc.
Category: otc | Type: HUMAN OTC DRUG LABEL
Date: 20160316

ACTIVE INGREDIENTS: DIMETHICONE 180 mg/1 1
INACTIVE INGREDIENTS: FD&C YELLOW NO. 6; GELATIN; GLYCERIN

Active Ingredient

(in each softgel)

Simethicone 180mg

Purpose

Anti-gas

Use

relieves bloating, pressure or fullness commonly referred to as gas

Stop use and ask a doctor if

condition persists

Directions

- swallow one or two softgels after a meal
- do not exceed two softgels per day except under the advice and supervision of a physician

Other Information

store at room temperature 59º - 86ºF (15º - 30ºC)

Inactive Ingredients

FD&C Yellow No. 6, Gelatin, Glycerin, White Edible Ink

Questions?

Call toll-free 1-855-727-4277